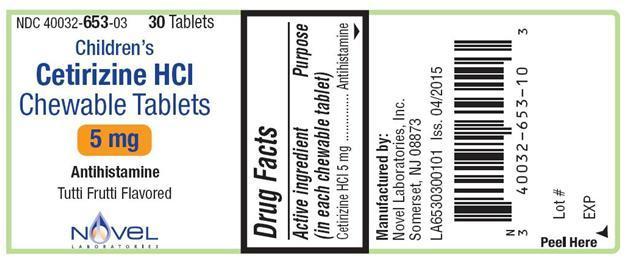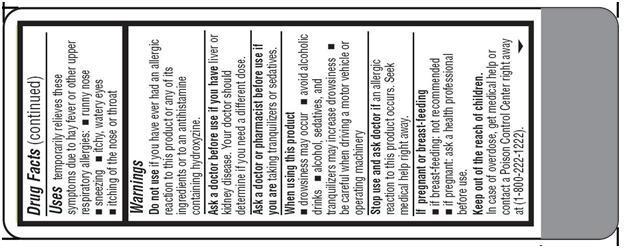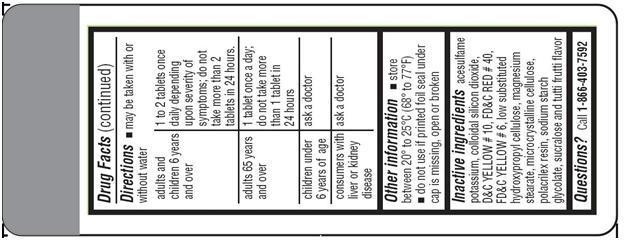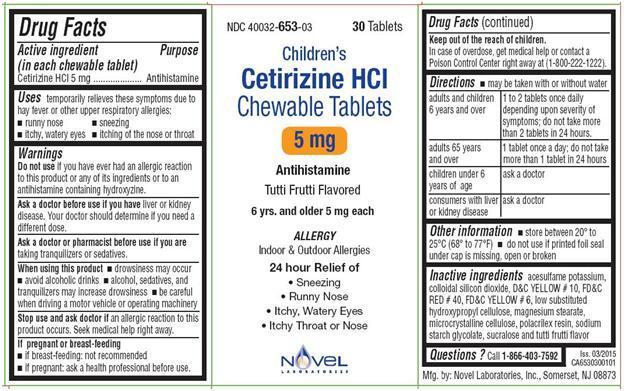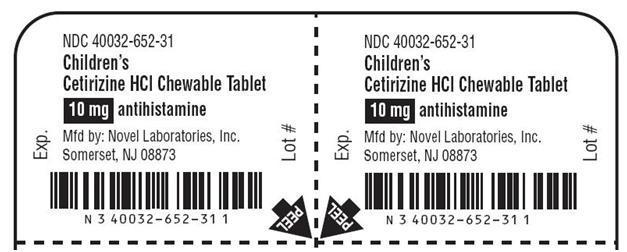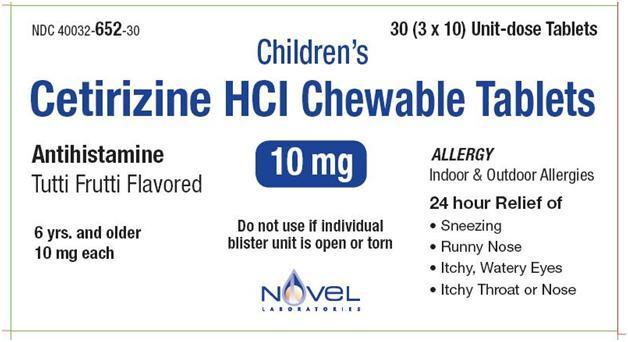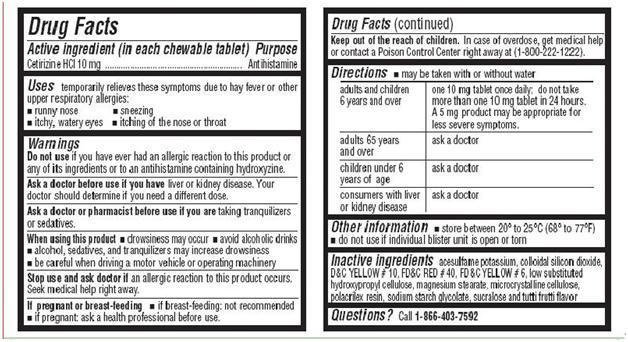 DRUG LABEL: Cetirizine Hydrochloride
NDC: 40032-653 | Form: TABLET, CHEWABLE
Manufacturer: Novel Laboratories, Inc.
Category: otc | Type: HUMAN OTC DRUG LABEL
Date: 20191220

ACTIVE INGREDIENTS: CETIRIZINE HYDROCHLORIDE 5 mg/1 1
INACTIVE INGREDIENTS: CELLULOSE, MICROCRYSTALLINE; HYDROXYPROPYL CELLULOSE, LOW SUBSTITUTED; POLACRILIN; ACESULFAME POTASSIUM; SODIUM STARCH GLYCOLATE TYPE A POTATO; SILICON DIOXIDE; SUCRALOSE; MAGNESIUM STEARATE; D&C YELLOW NO. 10; FD&C RED NO. 40; FD&C YELLOW NO. 6

Cetirizine Hydrochloride Chewable Tablets

Active Ingredient in each chewable tablet

For 5 mg:

Cetirizine hydrochloride 5 mg

For 10 mg:

Cetirizine hydrochloride 10 mg

PURPOSE

Antihistamine

Uses

Temporarily relieves these symptoms due to hay fever or other upper respiratory allergies:

- runny nose
- sneezing
- itchy, watery eyes
- itching of the nose or throat

WARNINGS

Do not use if you have ever had an allergic reactions to this product or any of its ingredients or to an antihistamine containing hydroxyzine.

Ask a doctor before use if you have

liver or kidney disease. Your doctor should determine if you need a different dose.

Ask a doctor or pharmacist before use

if you are taking tranquilizers or sedatives.

When using this product

- drowsiness may occur
- avoid alcoholic drinks
- alcohol, sedatives, and tranquilizers may increase drowsiness
- be careful when driving a motor vehicle or operating machinery

Stop use and ask doctor if

an allergic reaction to this product occurs. Seek medical help right away.

If pregnant or breast-feeding

- if breast-feeding: not recommended
- if pregnant: ask a health professional before use.

Keep out of the reach of children

In case of overdose, get medical help or contact a Poison Control Center right away at (1-800-222-1222).

Directions

- may be taken with or without water

For Cetirizine Hydrochloride Chewable Tablets, 5 mg

adults and children 6 years | 1 to 2 tablets once daily depending upon severity of symptoms; do not take
and over | more than 2 tablets in 24 hours.
adults 65 years and over | 1 tablet once a day; do not take more than 1 tablet in 24 hours
children under 6 years of | ask a doctor
age
consumers with liver or | ask a doctor
kidney disease

For Cetirizine Hydrochloride Chewable Tablets, 10 mg

adults and children 6 | one 10 mg tablet once daily; do not take more than one 10 mg tablet in 24 hours. A
years and over | 5 mg product may be appropriate for less severe symptoms.
adults 65 years and | ask a doctor
over
children under 6 years of age | ask a doctor
consumers with liver | ask a doctor
or kidney disease

Other information

- store between 20° to 25°C (68° to 77°F)
- Do not use if individual blister unit is open or torn

Inactive Ingredients

acesulfame potassium, colloidal silicon dioxide, D&C YELLOW # 10, FD&C RED # 40, FD&C YELLOW # 6, low substituted hydroxypropyl cellulose, magnesium stearate, microcrystalline cellulose, polacrilex resin, sodium starch glycolate, sucralose and tutti frutti flavor

QUESTIONS

Call 1-866-403-7592

Manufactured by:

Novel Laboratories, Inc.

Somerset, NJ 08873

PACKAGE LABEL.PRINCIPAL DISPLAY PANEL

For 5 mg Allergy:

NDC 40032-653-03

Children's

Cetirizine Hydrochloride Chewable Tablets

5 mg

ALLERGY

Antihistamine

Indoor & Outdoor Allergies

Tutti-frutti Flavor

6 yrs. & older

30 CHEWABLE TABLETS

Container Label

Container Carton

For 10 mg Allergy:

NDC 40032-652-31

Children's

Cetirizine Hydrochloride Chewable Tablets

10 mg

ALLERGY

Antihistamine

Indoor & Outdoor Allergies

Tutti-frutti Flavor

6 yrs. & older

Blister Label

Blister Carton

NDC 40032-652-30